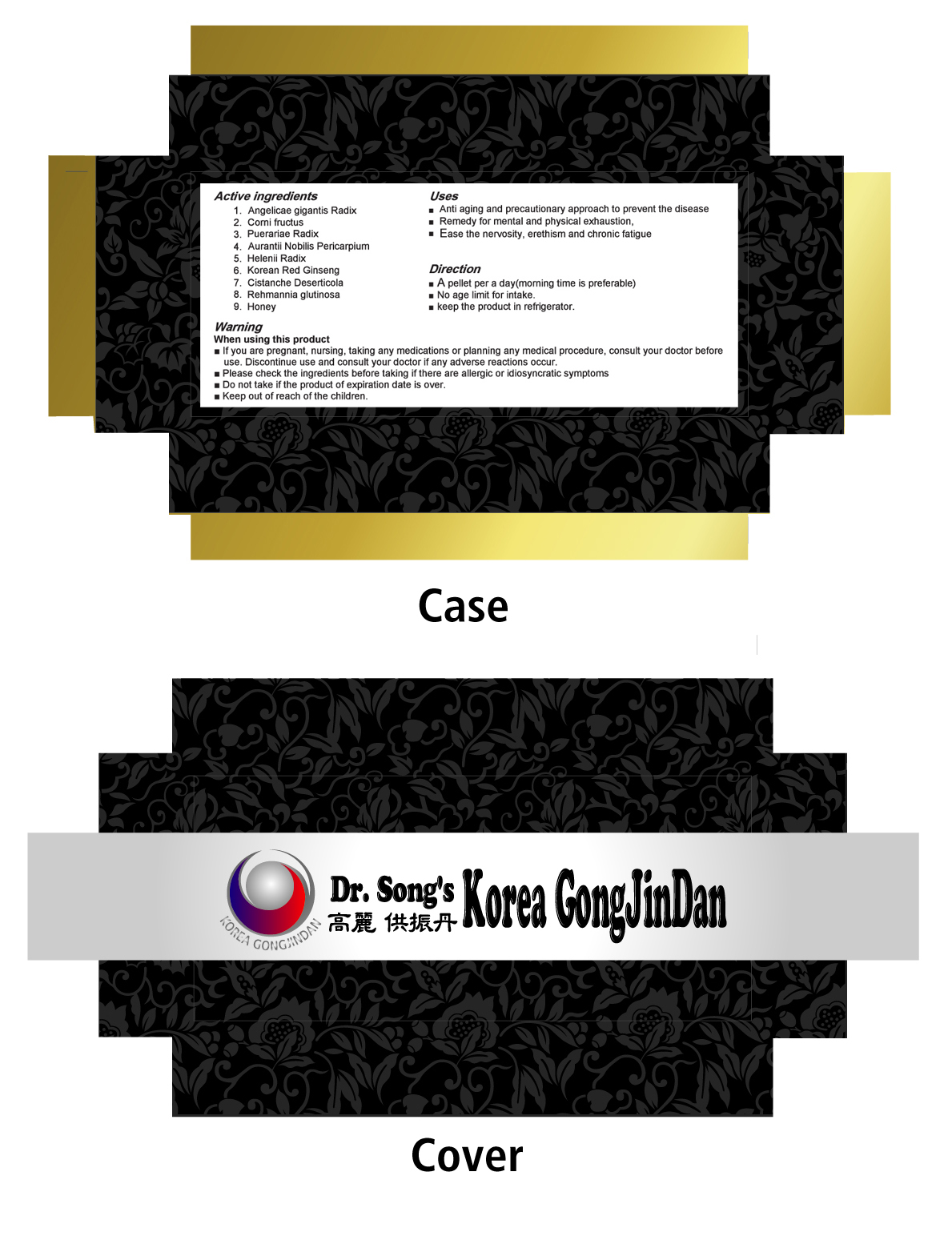 DRUG LABEL: Korea Gongjin-Dan
NDC: 76401-1001 | Form: PELLET
Manufacturer: Songjeongo OM Clinic
Category: otc | Type: HUMAN OTC DRUG LABEL
Date: 20120622

ACTIVE INGREDIENTS: PANAX GINSENG FRUIT 229 mg/4 g
INACTIVE INGREDIENTS: WATER; ANGELICA ARCHANGELICA ROOT; CORNUS OFFICINALIS FRUIT; PUERARIA MONTANA VAR. LOBATA ROOT; CITRUS AURANTIUM FRUIT RIND; KALOPANAX SEPTEMLOBUS BARK

Drug Facts

active ingredient: korean red ginseng

inactive ingredient: Water, Liriopis Tuber, Cervicornu Pavum, Angelicae gigantis Radix, Corni fructus, Gastrodiae Rhizoma, Puerariae Radix, Aurantii Nobilis Pericarpium, Maximowicziae Fructus, Helenii Radix,
Aquilaiae lignum

PURPOSE

■Improve virility, male potency
■ Anti aging and precautionary approach to prevent the disease
■ Fast recovery from aftereffects from surgery and illness.
■ Remedy for mental and physical exhaustion,
■ Cure the innate aphylaxis
■ Alleviate the sluggish and tingling sense raised by circulatory disorder
■ Ease mental and emotional disorder caused by poor stamina and repressed stress.
■ Ease the nervosity, erethism and chronic fatigue
■ Remedy palpitation and insomnia

keep out of reach of the children

INDICATIONS AND USAGE

■ A pellet per a day(morning time is preferable), chewing a pellet with lukewarm
drinking water is recommended
■ No age limit for intake.
■ keep the product in refrigerator.

When using this product
■ If you are pregnant, nursing, taking any medications or planning any medical procedure, consult your doctor before
use. Discontinue use and consult your doctor if any adverse reactions occur.
■ Please check the ingredients before taking if there are allergic or idiosyncratic symptoms
■ Do not take if the product of expiration date is over

DOSAGE AND ADMINISTRATION

■ No any specific food is prohibited during dosage except for alcoholic beverage or
Mung beans and it's processed foods if possible.